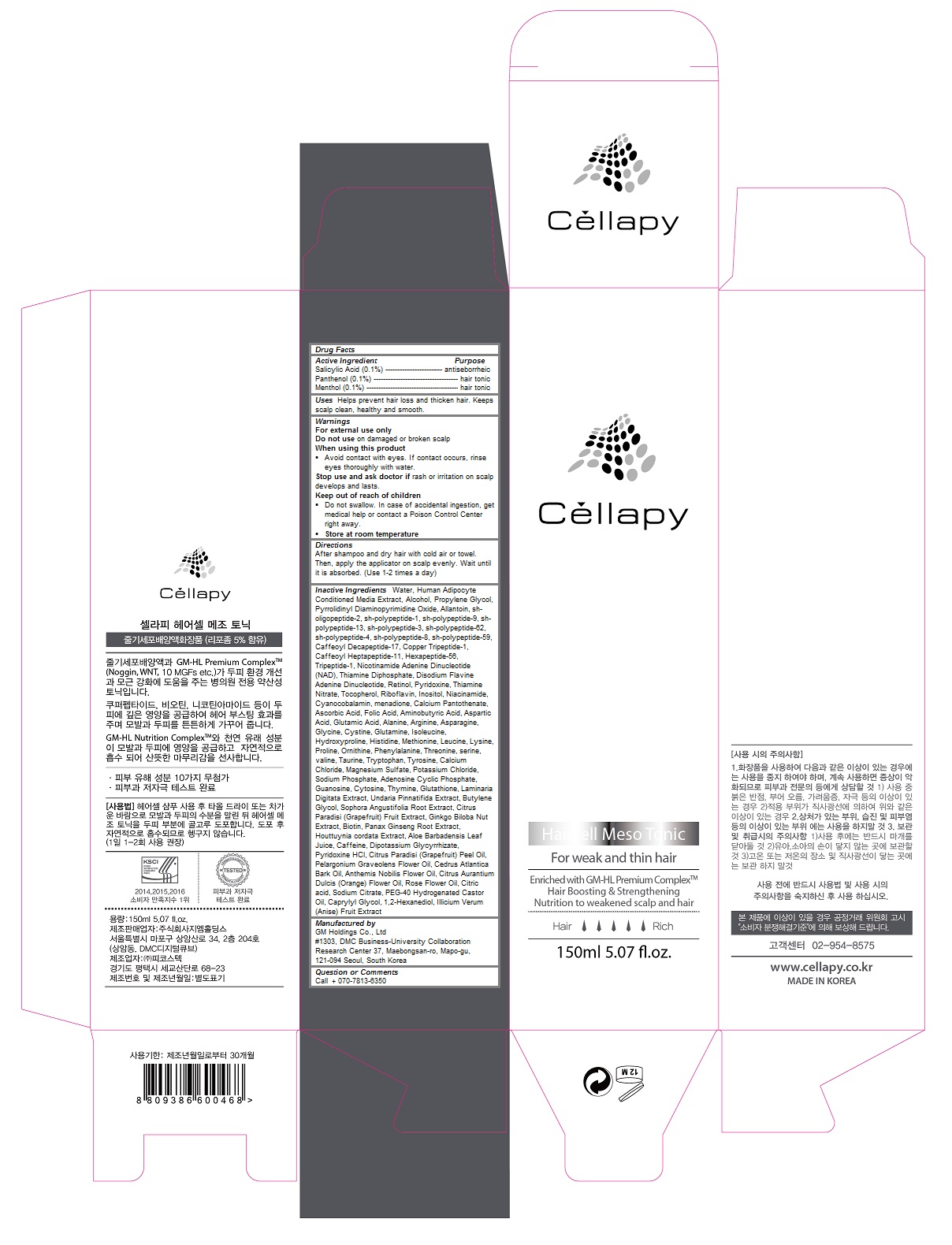 DRUG LABEL: Cellapy Haircell Meso Tonic
NDC: 69278-106 | Form: LIQUID
Manufacturer: Gm Holdings Co., Ltd
Category: otc | Type: HUMAN OTC DRUG LABEL
Date: 20200121

ACTIVE INGREDIENTS: SALICYLIC ACID 0.001 1/150 mL; PANTHENOL 0.001 1/150 mL; MENTHOL 0.001 1/150 mL
INACTIVE INGREDIENTS: WATER; ALCOHOL; PROPYLENE GLYCOL; PYRROLIDINYL DIAMINOPYRIMIDINE OXIDE; ALLANTOIN; MECASERMIN; BASIC FIBROBLAST GROWTH FACTOR (HUMAN); HUMAN NOGGIN; FIBROBLAST GROWTH FACTOR 7; BECAPLERMIN; PREZATIDE COPPER; PREZATIDE; NADIDE; COCARBOXYLASE; FLAVIN ADENINE DINUCLEOTIDE; RETINOL; PYRIDOXINE; THIAMINE MONONITRATE; TOCOPHEROL; RIBOFLAVIN; INOSITOL; NIACINAMIDE; CYANOCOBALAMIN; MENADIONE; CALCIUM PANTOTHENATE; ASCORBIC ACID; FOLIC ACID; .GAMMA.-AMINOBUTYRIC ACID; ASPARTIC ACID; GLUTAMIC ACID; ALANINE; ARGININE; ASPARAGINE; GLYCINE; CYSTINE; GLUTAMINE; ISOLEUCINE; HYDROXYPROLINE; HISTIDINE; METHIONINE; LEUCINE; LYSINE; PROLINE; ORNITHINE; PHENYLALANINE; THREONINE; SERINE; VALINE; TAURINE; TRYPTOPHAN; TYROSINE; CALCIUM CHLORIDE; MAGNESIUM SULFATE, UNSPECIFIED FORM; POTASSIUM CHLORIDE; SODIUM PHOSPHATE; ADENOSINE CYCLIC PHOSPHATE; GUANOSINE; CYTOSINE; THYMINE; GLUTATHIONE; LAMINARIA DIGITATA; UNDARIA PINNATIFIDA; BUTYLENE GLYCOL; SOPHORA FLAVESCENS ROOT; GRAPEFRUIT; GINKGO BILOBA SEED; BIOTIN; ASIAN GINSENG; HOUTTUYNIA CORDATA FLOWERING TOP; ALOE VERA LEAF; CAFFEINE; GLYCYRRHIZINATE DIPOTASSIUM; PYRIDOXINE HYDROCHLORIDE; GRAPEFRUIT OIL; PELARGONIUM GRAVEOLENS FLOWER OIL; CEDRUS ATLANTICA BARK OIL; CHAMAEMELUM NOBILE FLOWER OIL; CITRUS SINENSIS FLOWER OIL; CITRIC ACID MONOHYDRATE; SODIUM CITRATE, UNSPECIFIED FORM; POLYOXYL 40 HYDROGENATED CASTOR OIL; CAPRYLYL GLYCOL; 1,2-HEXANEDIOL; STAR ANISE FRUIT

Cellapy Haircell Meso Tonic